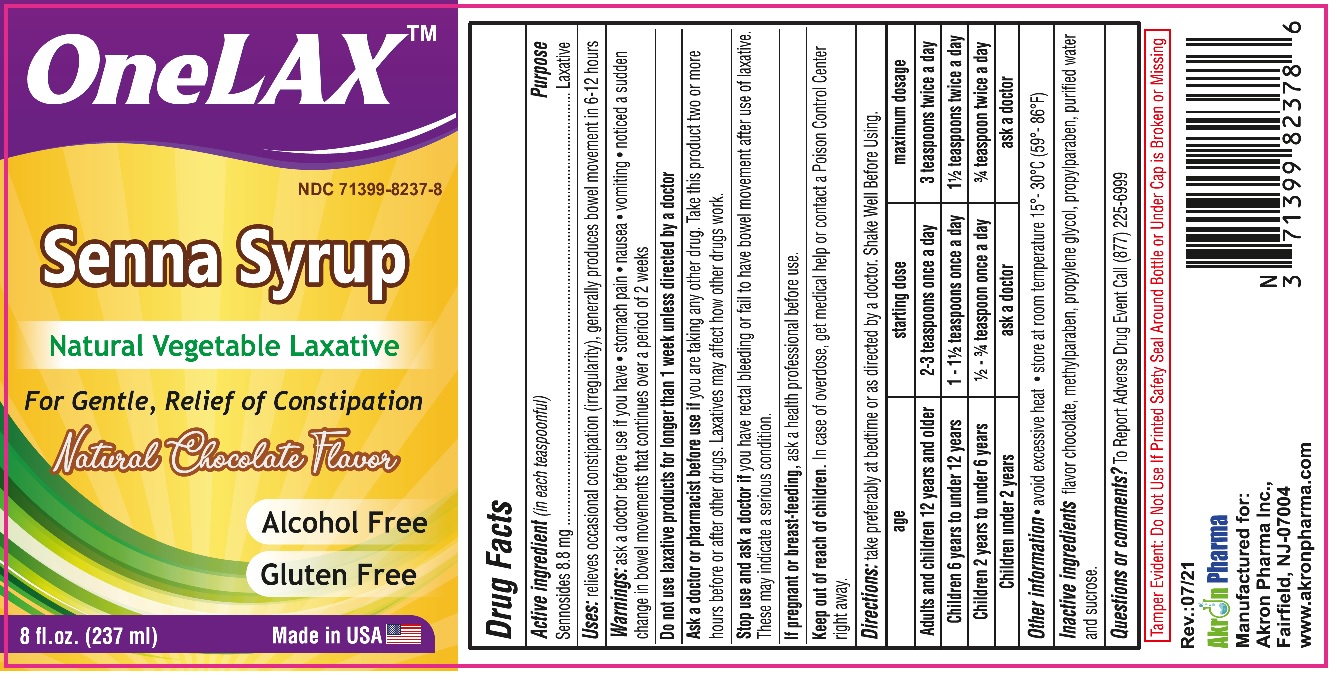 DRUG LABEL: SENNA
NDC: 71399-8237 | Form: SYRUP
Manufacturer: Akron Pharma Inc.
Category: otc | Type: HUMAN OTC DRUG LABEL
Date: 20230318

ACTIVE INGREDIENTS: SENNOSIDES A AND B 417.12 mg/237 mL
INACTIVE INGREDIENTS: METHYLPARABEN; PROPYLENE GLYCOL; PROPYLPARABEN; WATER; SUCROSE

SENNA SYRUP
Natural Vegitable Lexative

Active Ingredient

Active ingredient (in each 5 ml) purpose
Sennosides 8.8 mg …………………………................Laxative

Uses

relieves occasional constipation (irregularity)
generally causes bowel movement in 6 to 12 hours

Directions

shake well before use
take preferably at bedtime or as directed by a doctor

age | starting dose | maximum dosage
Mulls and children 12 yeart and older | 2-3 teaspoons once a day | 3 teaspoons twice a day
Children 6 years to under 12 yeart | 1 -11> teaspoons once a day | 11> teaspoons twice a day
Children 2 yeart to under 6 yeart | l> -¾teaspoon once a day | ¾ teaspoon twice a day
Children under 2 years | ask a doctor | ask a doctor

Warnings

ask a doctor betore use rt you have • stomach pain • nausea • vomiting • noticed a sudden change in bowel movements that continues over a period of 2 weeks

Do not use laxative produe1s for longer than 1 week unless directed by a doctor

Other Information

- Avoid accessive heat. Store at room temperature 15°-30°C (59°-86°F)

Inactive Ingredients

Mythylparaben, Propylene Glycol, Propylparaben, Purified Water, Sucrose

KEEP OUT OF REACH OF CHILDREN SECTION

In case of accidental overdose, get medical help or contact a Poison Control Center immediately

Questions?

To Report Adverse Drug Event Call 1(877) 225-6999

Manufactured for:

Akron Pharma Inc.,

Fairfield, NJ-07004